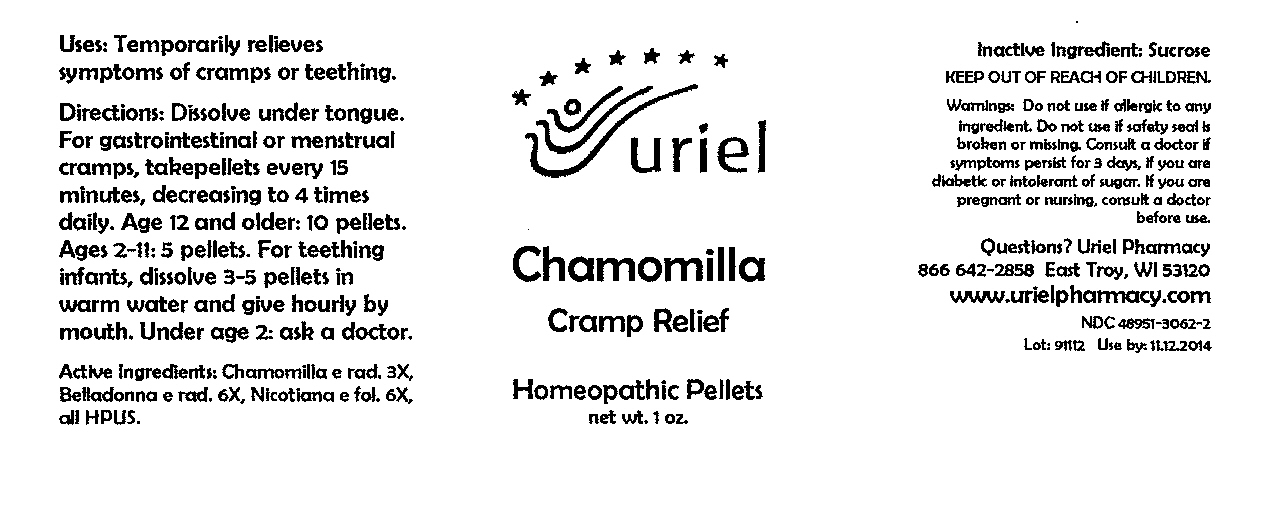 DRUG LABEL: Chamomila Cramp Relief 
NDC: 48951-3062 | Form: PELLET
Manufacturer: Uriel Pharmacy Inc
Category: homeopathic | Type: HUMAN OTC DRUG LABEL
Date: 20091201

ACTIVE INGREDIENTS: MATRICARIA RECUTITA 3 [hp_X]/1 1; ATROPA BELLADONNA ROOT 6 [hp_X]/1 1; TOBACCO LEAF 6 [hp_X]/1 1
INACTIVE INGREDIENTS: SUCROSE

Chamomilla Cramp Relief Pellets - 1 oz.

Purpose

Uses: Temporarily relieves symptoms of cramps or teething.

Dosage & Administration

Directions: Dissolve under tongue. For gastrointestinal or menstrual cramps, take pellets every 15 minutes, decreasing to 4 times daily. Age 12 and older: 10 pellets. Ages 2-11: 5 pellets. For teething infants, dissolve 3-5 pellets in warm water and give hourly by mouth. Under age 2: ask a doctor.

OTC-Active Ingredient

Active Ingredients: Chamomilla e rad. 3X, Belladonna e rad. 6X, Nicotiana e fol. 6X, all HPUS.

Inactive Ingredient

Inactive Ingredient: Sucrose

Keep out of reach of children

Do not use section

Warnings:Do not use if allergic to any ingredient. Do not use if safety seal is broken or missing.

Ask doctor section

Consult a doctor if symptoms persist for 3 days, if you are diabetic or intolerant of sugar.

Pregnancy or breast feeding section

If you are pregnant or nursing, consult a doctor before use.

Questions section

Questions? Uriel Pharmacy

866 642-2858 East Troy, WI 53120

www.urielpharmacy.com

NDC 48951-3062-2

Principal Display Panel

Chamomilla

Cramp Relief

Homeopathic Pellets

net wt. 1 oz.